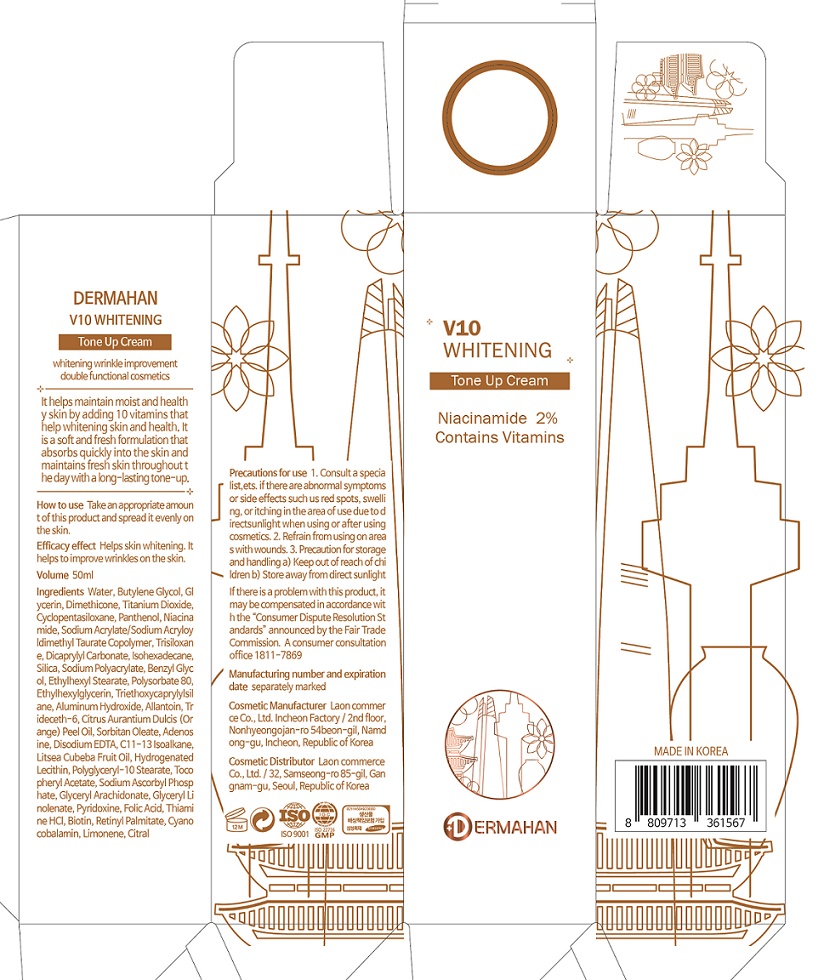 DRUG LABEL: DERMAHAN V10 WHITENING TONE UpCREAM
NDC: 82083-0014 | Form: CREAM
Manufacturer: LAON COMMERCE co ltd
Category: otc | Type: HUMAN OTC DRUG LABEL
Date: 20230306

ACTIVE INGREDIENTS: ADENOSINE 0.04 g/100 mL; NIACINAMIDE 2 g/100 mL
INACTIVE INGREDIENTS: WATER

ACTIVE INGREDIENT

Adenosine, Niacinamide

INACTIVE INGREDIENT

Water
Butylene Glycol
Glycerin
Dimethicone
Titanium Dioxide
Cyclopentasiloxane
Panthenol
Sodium Acrylate/Sodium Acryloyldimethyl Taurate Copolymer
Trisiloxane
Dicaprylyl Carbonate
Isohexadecane
Dimethiconol
Silica
Sodium Polyacrylate
Benzyl Glycol
Ethylhexyl Stearate
Polysorbate 80
Ethylhexylglycerin
Triethoxycaprylylsilane
Aluminum Hydroxide
Allantoin
Trideceth-6
Citrus Aurantium Dulcis (Orange) Peel Oil
Sorbitan Oleate
Disodium EDTA
C11-13 Isoalkane
Litsea Cubeba Fruit Oil
Hydrogenated Lecithin
Polyglyceryl-10 Stearate
Tocopheryl Acetate
Sodium Ascorbyl Phosphate
Glyceryl Arachidonate
Glyceryl Linolenate
Pyridoxine
Folic Acid
Thiamine HCl
Biotin
Retinyl Palmitate
Cyanocobalamin
Limonene
Citral

PURPOSE

whitening, wrinkle care

KEEP OUT OF REACH OF THE CHILDREN

INDICATIONS AND USAGE

Take an appropriate amount of this product and spread it evenly on the skin

WARNINGS

1. Consult a specialist, if there are abnormal symptoms or side effects such us red spots, swelling, or itching in the area of use due to direct sunlight when using or after using cosmetics.

2. Refrain from using on area s with wounds.

3. Precaution for storage and handling a) Keep out of reach of children b) Store away from direct sunlight

DOSAGE AND ADMINISTRATION

topical use only